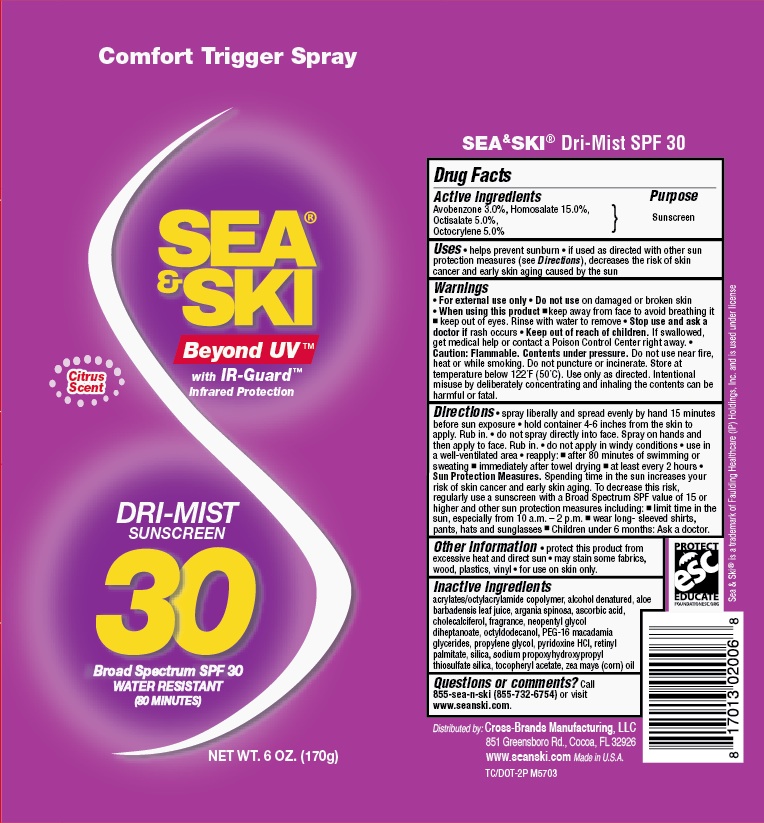 DRUG LABEL: General Protection
NDC: 71153-2006 | Form: AEROSOL, SPRAY
Manufacturer: Cross-Brand Manufacturing
Category: otc | Type: HUMAN OTC DRUG LABEL
Date: 20190108

ACTIVE INGREDIENTS: OCTISALATE 5 g/1 g; OCTOCRYLENE 5 g/1 g; AVOBENZONE 3 g/1 g; HOMOSALATE 15 g/1 g
INACTIVE INGREDIENTS: ALOE VERA LEAF 0.1 g/1 g

Sea Ski SPF 30 CSpray